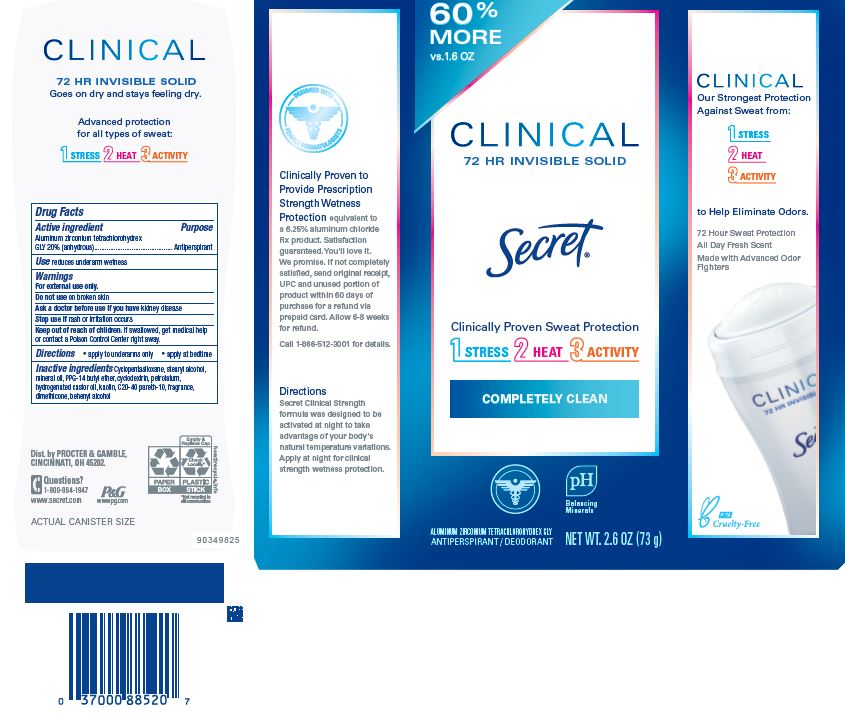 DRUG LABEL: Secret Clinical Completely Clean Invisible
NDC: 69423-714 | Form: STICK
Manufacturer: The Procter & Gamble Manufacturing Company
Category: otc | Type: HUMAN OTC DRUG LABEL
Date: 20251231

ACTIVE INGREDIENTS: ALUMINUM ZIRCONIUM TETRACHLOROHYDREX GLY 20 g/100 g
INACTIVE INGREDIENTS: CYCLOPENTASILOXANE; CYCLODEXTRINS; STEARYL ALCOHOL; MINERAL OIL; PPG-14 BUTYL ETHER; KAOLIN; PETROLATUM; HYDROGENATED CASTOR OIL; C20-40 PARETH-10; DIMETHICONE; BEHENYL ALCOHOL

Secret® Clinical Shower Fresh Invisible

Drug Facts

Active ingredient

Aluminum zirconium tetrachlorohydrex Gly 20% (anhydrous)

Purpose

Antiperspirant

Use

- reduces underarm wetness

Warnings

For external use only.

Do not use on broken skin

Ask a doctor before use if you have kidney disease

Stop use if rash or irritation occurs

Keep out of reach of children. If swallowed, get medical help or contact a Poison Control Center right away.

Directions

- Apply at bedtime, to underarms only.

Inactive ingredients

cyclopentasiloxane, stearyl alcohol, mineral oil, PPG-14 butyl ether, cyclodextrin, petrolatum, hydrogenated castor oil, kaolin, C20-40 pareth-10, fragrance, dimethicone, behenyl alcohol

Questions?

1-800-964-1947

Dist. by PROCTER & GAMBLE,
CINCINNATI, OH 45202.

PRINCIPAL DISPLAY PANEL - 73 g Carton

Secret ®
CLINICAL

72 HR INVISIBLE SOLID

COMPLETELY CLEAN

ALUMINUM ZIRCONIUM TETRACHLOROHYDREX GLY
ANTIPERSPIRANT / DEODORANT

NET WT. 2.6 OZ (73 g)